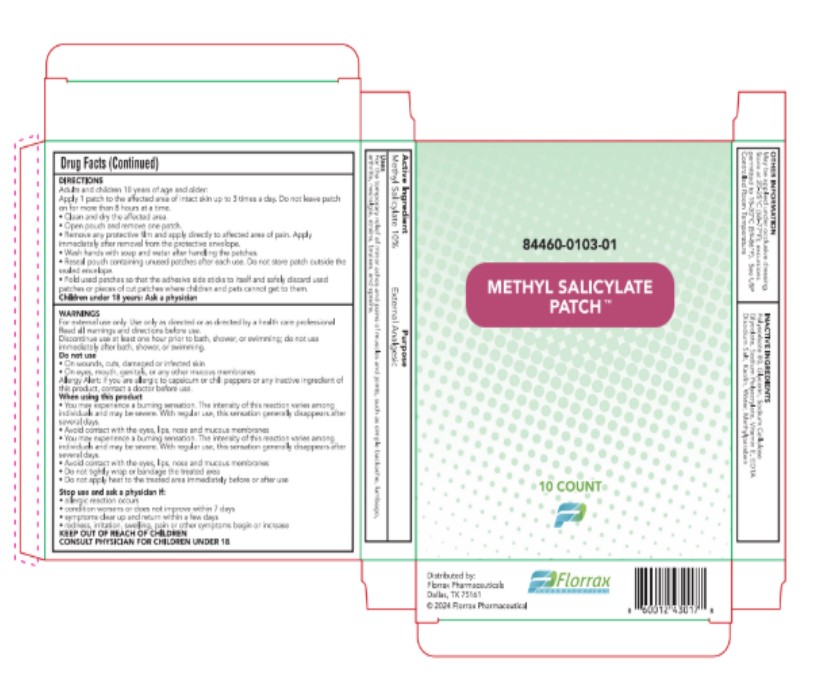 DRUG LABEL: Methyl Salicylate
NDC: 84460-103 | Form: PATCH
Manufacturer: Florrax Pharmaceutical Corp.
Category: otc | Type: HUMAN OTC DRUG LABEL
Date: 20250210

ACTIVE INGREDIENTS: METHYL SALICYLATE 10 g/100 g
INACTIVE INGREDIENTS: EDETATE DISODIUM; KAOLIN; METHYLPARABEN; SODIUM POLYACRYLATE (8000 MW); CARBOXYMETHYLCELLULOSE SODIUM; GLYCERIN; WATER; POLYSORBATE 80; ALPHA-TOCOPHEROL

Directions

Adults and children 18 years of age and older:

Apply 1 patch to the affected area of intact skin up to 3 times a day. Do not leave patch on for more than 8 hours at a time.

- Clean and dry affected area
- Open pouch and remove one patch
- Remove any protective film and apply directly to affected area of pain. Apply immediately after removal form the protective envelope.
- Wash hands with soap and water after handling the patches.
- Reseal pouch containing unused patches after each use. Do not store patch outside the sealed envelope.

Fold used patches so that the adhesive side sticks to itself and safely discard used patches of pieces of cut patches where children and pets cannot get to them.

Children under 18 years: Ask a physician

Purpose

External Analgesic

Uses

For the temporary relief of minor aches and pains of muscles and joints, such as simple backache, lumbago, arthritis, neuralgia, strains, bruises, and sprains.

Warnings

For external use only. Use only as directed or as directed by a healthcare professional. Read all warnings and directions before us. Discontinue use at least one hour prior to bath, shower, or swimming; do not use immediately after bath, shower, or swimming.

Do not use

- On wounds, cuts, damaged or infected skin
- On eyes, mouth, genitals, or any other mucous membranes

Allergy Alert: if you are allergic to capsicum or chili peppers or any inactive ingredient of this product, contact a doctor before use.

When using this product

- You may experience a burning sensation. The intensity of this reaction varies among individuals and may be severe. With regular use, this sensatoin generally disappears after several days.
- Avoid contact with the eyes, lips, nose and mucous membranes
- You may experiences a burning sensation. The intensity of this reaction varies among individuals and may be severe. With regular use, this sensation generally disappears after several days.
- Avoid contact with the eyes, lips, nose and mucous membranes
- Do not tightly wrap or bandage the treated area
- Do no apply heat to the treated area immediately before or after use

Stop use and ask a physician if:

- allergic reaction occurs
- condition worsens or does not improve within 7 days
- symptoms clear up and return within a few days
- redness, irritation, swelling, pain or other symptoms begin or increase

KEEP OUT OF REACH OF CHILDREN

CONSULT PHYSICIAN FOR CHILDREN UNDER 18.

Active Ingredient

Methyl Salicylate 10%

Other Information

May be applied under occlusive dressing.

Store at 20-25°C (68-77°F); excursions permitted to 15-30°C(59-86°F). See USP Controlled Room Temparature

Inactive Ingredients

Polysorbate 80, Glycerin, Sodium Cellulose Glycolate, Sodium Polyacrylate, Vitamin E, EDTA Disodium Salt, Kaolin, Water, Methylparaben